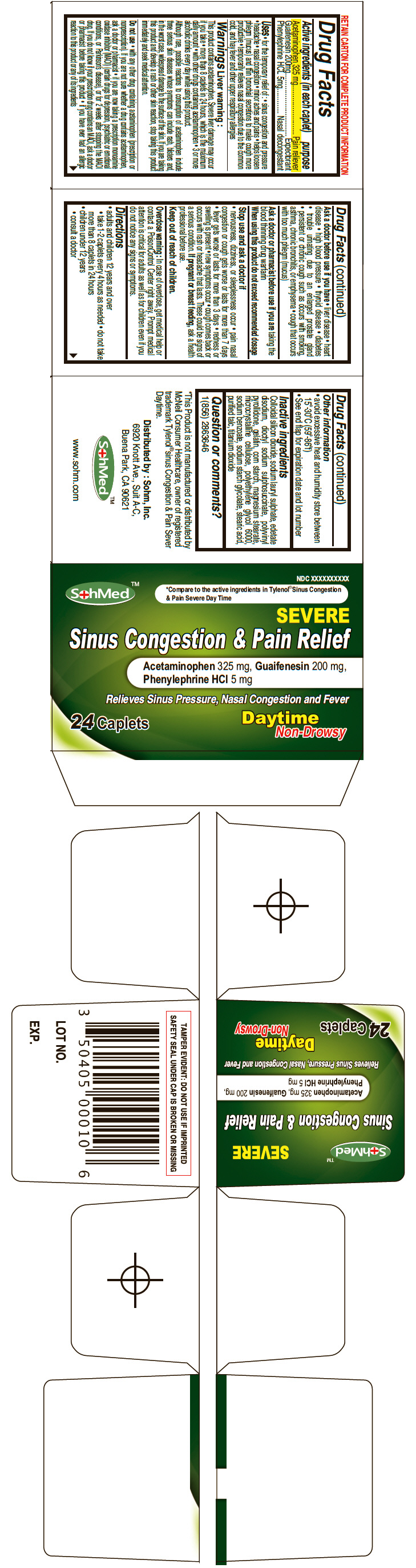 DRUG LABEL: SohMed Sinus
NDC: 50405-009 | Form: TABLET
Manufacturer: Sohm Inc.
Category: otc | Type: HUMAN OTC DRUG LABEL
Date: 20130821

ACTIVE INGREDIENTS: Acetaminophen 325 mg/1 1; Guaifenesin 200 mg/1 1; Phenylephrine Hydrochloride 5 mg/1 1
INACTIVE INGREDIENTS: SILICON DIOXIDE; SODIUM LAURYL SULFATE; EDETATE DISODIUM; DI-2-HEXYL SODIUM SULFOSUCCINATE; STARCH, CORN; POVIDONE K90; GELATIN; MAGNESIUM STEARATE; CELLULOSE, MICROCRYSTALLINE; POLYETHYLENE GLYCOL 6000; SODIUM BENZOATE; SODIUM STARCH GLYCOLATE TYPE A CORN; STEARIC ACID; TALC; TITANIUM DIOXIDE

SohMed™ Sinus

Drug Facts

ACTIVE INGREDIENT

Active ingredients (in each caplet) | purpose
Acetaminophen 325 mg | Pain reliever
Guaifenesin 200mg | Expectorant
Phenylephrine HCL 5mg | Nasal decongestant

Uses

- for the temporary relief of :
  - sinus congestion and pressure
  - headache
  - nasal congestion
  - minor aches and pains
  - helps loosen phlegm (mucus) and thin bronchial secretions to make cough more productive
- temporarily relieves nasal congestion due to the common cold, and hay fever and other upper respiratory allergies

Warnings

Liver warning

This product contains acetaminophen. Severe liver damage may occur if you take

- more than 8 caplets in 24 hours, which is the maximum daily amount
- with other drugs containing acetaminophen
- 3 or more alcoholic drinks every day while using this product.

Although rare, possible reactions to consumption of acetaminophen include three serious skin diseases whose symptoms can include rash, blisters and, in the worst case, widespread damage to the surface of the skin. If you are taking this product and develop a rash or other skin reaction, stop taking this product immediately and seek medical attention.

Do not use

- with any other drug containing acetaminophen (prescription or nonprescription). If you are not sure whether a drug contains acetaminophen, ask a doctor or pharmacist
- if you are now taking a prescription monoamine oxidase inhibitor (MAOI) (certain drugs for depression, psychiatric or emotional conditions, or Parkinson's disease), or for 2 weeks after stopping the MAOI drug. If you do not know if your prescription drug contains an MAOI, ask a doctor or pharmacist before taking this product
- if you have ever had an allergic reaction to this product or any of its ingredients

Ask a doctor before use if you have

- liver disease
- heart disease
- high blood pressure
- thyroid disease
- diabetes
- trouble urinating due to an enlarged prostate gland
- persistent or chronic cough such as occurs with smoking, asthma, chronic bronchitis, or emphysema
- cough that occurs with too much phlegm (mucus)

Ask a doctor or pharmacist before use if you are taking the blood thinning drug warfarin

When using this product do not exceed recommended dosage

Stop use and ask a doctor if

- nervousness, dizziness, or sleeplessness occur
- pain nasal congestion or cough gets worse or lasts for more than 7 days
- fever gets worse or lasts for more than 3 days
- redness or swelling is present
- new symptoms occur
- cough comes back or occurs with rash or headache that lasts.
  These could be signs of a serious condition.

PREGNANCY OR BREAST FEEDING

If pregnant or breast feeding, ask a health professional before use.

Keep out of reach of children.

Overdose warning

In case of overdose, get medical help or contact a PoisonControl Center right away. Prompt medical attention is critical for adults as well as for children even if you do not notice any signs or symptoms.

Directions

- adults and children 12 years and over
  - take 1-2 caplets every 4 hours as needed
  - do not take more than 8 caplets in 24 hours
- children under 12 years
  - consult a doctor

Other information

- avoid excessive heat and humidity store between 15°-30°C (59°-86°f)
- See end flap for expiration date and lot number

Inactive ingredients

Colloidal silicon dioxide, sodium lauryl sulphate, edetate disodium, dioctyl sodium sulphosuccinate, polyvinyl pyrollidone, gelatin, corn starch, magnesium stearate, microcrystalline cellulose, polyethylene glycol 6000, sodium benzoate, sodium starch glycolate, stearic acid, purified talc, titanium dioxide

Question or comments?

1(856) 2863646

Distributed by : Sohm, Inc.
6920 Knott Ave., Suit A-C,
Buena Park, CA 90621

PRINCIPAL DISPLAY PANEL - 24 Caplet Bottle Carton

SohMed™

NDC XXXXXXXXXX

*Compare to the active ingredients in Tylenol® Sinus Congestion
& Pain Severe Day Time

SEVERE
Sinus Congestion & Pain Relief

Acetaminophen 325 mg, Guaifenesin 200 mg,
Phenylephrine HCl 5 mg

Relieves Sinus Pressure, Nasal Congestion and Fever

24 Caplets

Daytime
Non-Drowsy